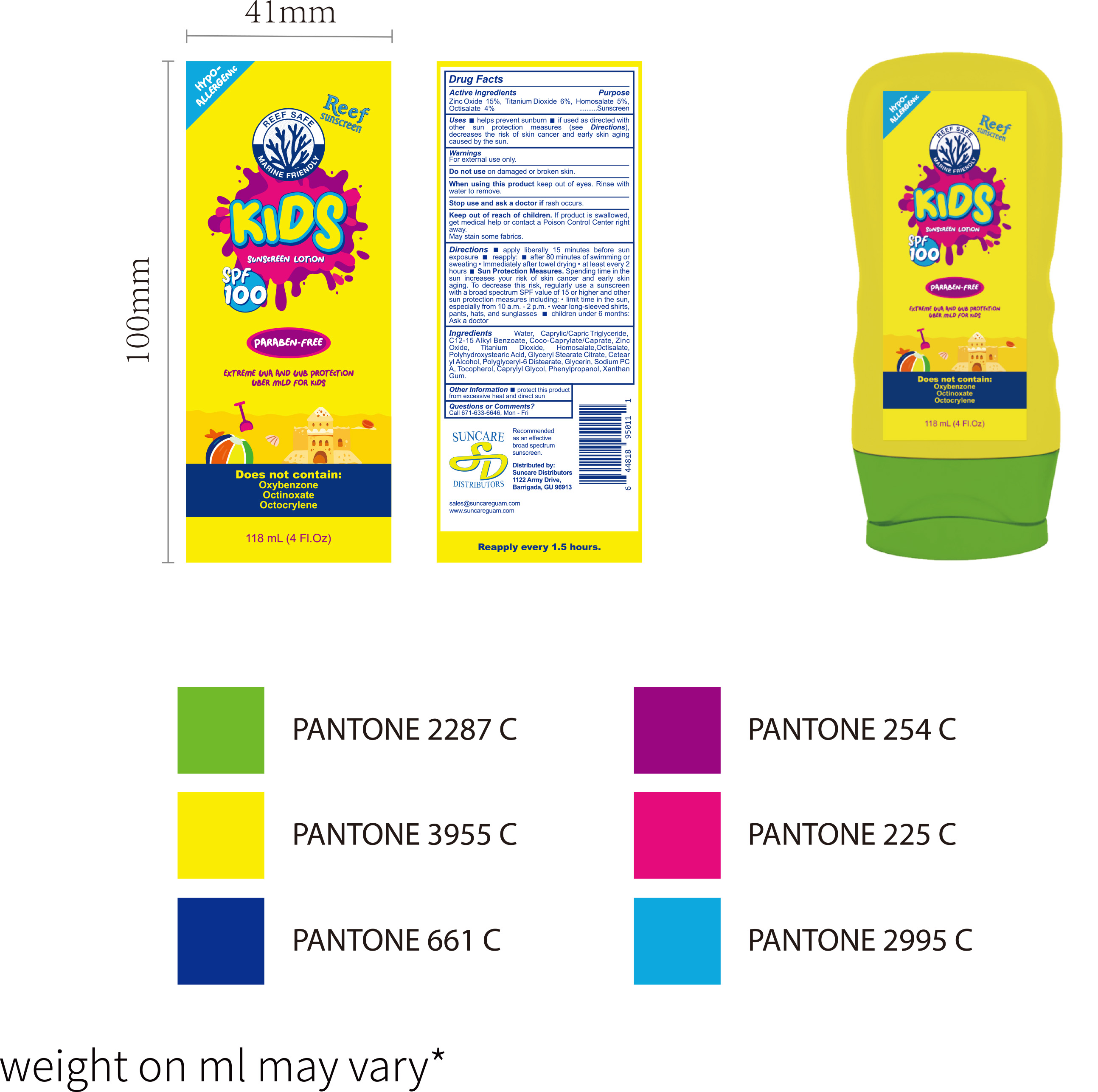 DRUG LABEL: Sunscreen Lotion118mL
NDC: 84938-013 | Form: LOTION
Manufacturer: Foshan Sugar Max Cosmetics CO.,Ltd
Category: otc | Type: HUMAN OTC DRUG LABEL
Date: 20251218

ACTIVE INGREDIENTS: TITANIUM DIOXIDE 0.06 g/1 mL; OCTISALATE 0.04 g/1 mL; ZINC OXIDE 0.15 g/1 mL; HOMOSALATE 0.05 g/1 mL
INACTIVE INGREDIENTS: C12-15 ALKYL BENZOATE; COCO-CAPRYLATE/CAPRATE; GLYCERYL STEARATE CITRATE; XANTHAN GUM; CAPRYLIC/CAPRIC TRIGLYCERIDE; POLYHYDROXYSTEARIC ACID (2300 MW); POLYGLYCERYL-6 DISTEARATE; CETEARYL ALCOHOL; SODIUM PCA; TOCOPHEROL; CAPRYLYL GLYCOL; PHENYLPROPANOL; AQUA; GLYCERIN

84938-013 Sunscreen Lotion

ACTIVE INGREDIENT

Zinc Oxide 15%,Titanium Dioxide 6%,Homosalate 5%, Octisalate 4%

PURPOSE

Sunscreen

INDICATIONS AND USAGE

Uses helps prevent sunburn if used as directed with other sun protection measures(see Directions) decreases the risk of skin cancer and early skin aging caused by the sun.

WARNINGS

For external use only.

Do not use on damaged or broken skin.

When using this product keep out of eyes. Rinse with water to remove.

Stop use and ask a doctor if rash occurs

Keep out of reach of children. lf product is swallowed get medical help or contact a Poison Control Center right away.
May stain some fabrics

DOSAGE AND ADMINISTRATION

Directions apply liberally 15 minutes before sun exposure m reapply: after 80 minutes of swimming or sweating "lmmediately after towel drying "at least every 2 hours m Sun Protection Measures. Spending time in the sun increases your risk of skin cancer andearly skin aging. To decrease this risk, regularly use a sunscreen with a broad spectrum SPF value of 15 or higher and othersun protection measures including:"limit time in the sun.especially from 10 a.m.-2 p.m..wear long-sleeved shirts pants, hats,and sunglasses children under 6 months Ask a doctor

INACTIVE INGREDIENT

Aqua (Water)
Caprylic/Capric Triglyceride
C12‑15 Alkyl Benzoate
Coco‑Caprylate/Caprate
Polyhydroxystearic Acid
Glyceryl Stearate Citrate
Cetearyl Alcohol
Polyglyceryl‑6 Distearate
Glycerin
Sodium PCA
Tocopherol (Vitamin E)
Caprylyl Glycol
Phenylpropanol
Xanthan Gum